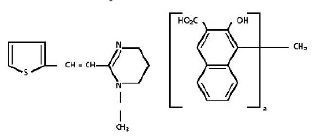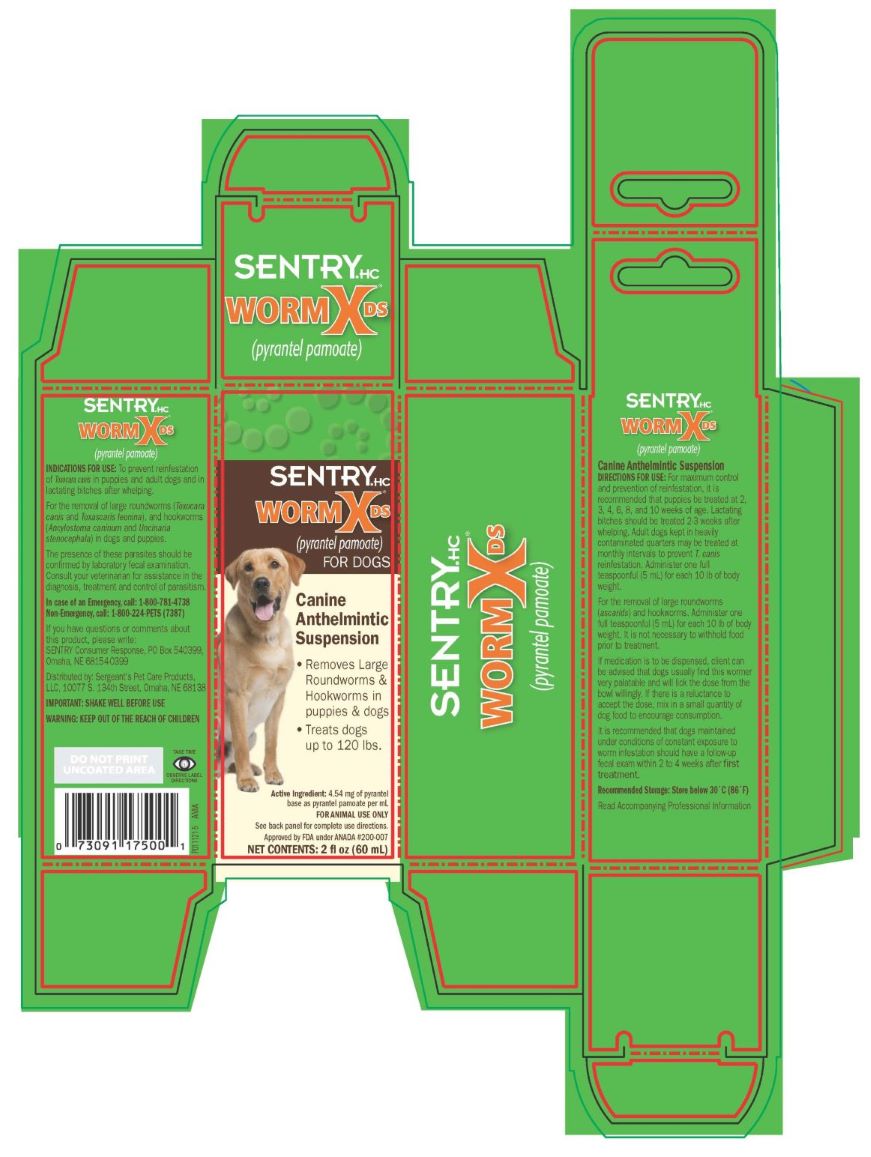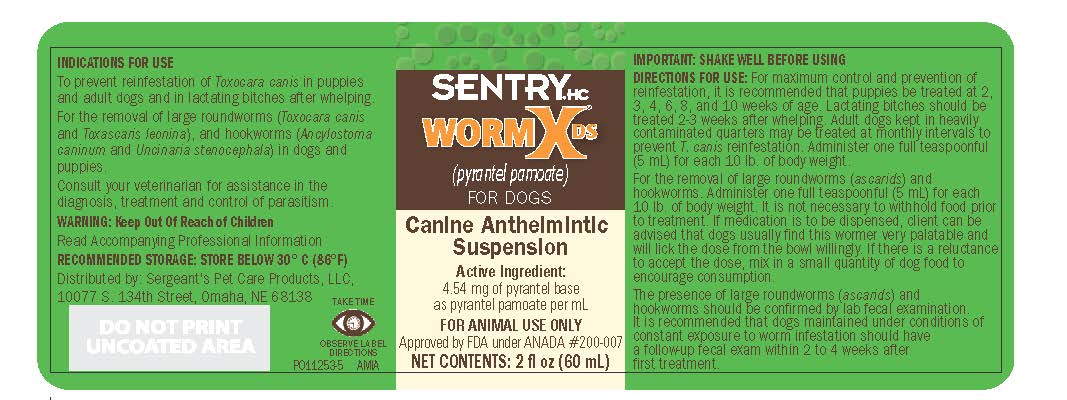 DRUG LABEL: Sentry HC Worm X DS
NDC: 21091-500 | Form: LIQUID
Manufacturer: Sergeant's Pet Care Products, LLC
Category: animal | Type: OTC ANIMAL DRUG LABEL
Date: 20231115

ACTIVE INGREDIENTS: Pyrantel Pamoate 4.54 mg/1 mL
INACTIVE INGREDIENTS: METHYLPARABEN SODIUM

Sentry HC Worm X DS
For Dogs(pyrantel pamoate)

INFORMATION FOR OWNERS/CAREGIVERS

Canine Anthelmintic Suspension

Approved by FDA under ANADA # 200-007

WormX DS is a suspension of pyrantel pamoate in a palatable butterscotch flavored vehicle. Each mL contains 4.54 mg of pyrantel base as pyrantel pamoate.

Pyrantel pamoate is a compound belonging to a family classified chemically as tetrahydropyrimidines. It is a yellow, water-insoluble crystalline salt of the tetrahydropyrimidine base and pamoic acid containing 34.7% base activity. The chemical structure and name are given below.

(E)-1,4,5,6-Tetrahydro-1-methyl-2-[2-thienyl) vinyl] pyrimidine 4,4' methylenebis [3-hydroxy-2-naphthoate](1:1)

INDICATIONS FOR USE:

WormX DS suspension is a highly palatable formulation intended as a single treatment for the removal of large roundworms (Toxocara canis and Toxacaris leonina), and hookworms (Ancylostoma caninum and Uncinaria stenocephala) in dogs and puppies.

WormX DS suspension may also be used to prevent reinfestation of Toxocara canis in puppies and adult dogs and in lactating bitches after whelping.

Consult your veterinarian for assistance in the diagnosis, treatment, and control of parasitism.

DOSAGE AND ADMINSITRATION:

Administer one full teaspoon (5 mL) for each 10 pounds of body weight (2.27 mg base per lb. of body weight). Although most dogs have been observed to find this formulation very palatable and willingly consume it undiluted, it may be necessary to mix a small quantity of formulation in the dog's normal ration to encourage consumption. Fasting prior to and after treatment is not necessary.

For maximum control and prevention of reinfestation, it is recommended that puppies be treated at 2, 3, 4, 6, 8 and 10 weeks of age. Lactating bitches should be treated 2-3 weeks after whelping. Adult dogs kept in heavily contaminated quarters may be treated at monthly intervals to prevent T. canis reinfestation.

CAUTION: THIS PRODUCT IS A SUSPENSION AND AS SUCH WILL SEPARATE. TO ENSURE UNIFORM RESUSPENSION AND TO ACHIEVE PROPER DOSAGE, IT IS EXTREMELY IMPORTANT THAT THE PRODUCT BE SHAKEN THOROUGHLY BEFORE EVERY USE.

SUMMARY OF SAFETY AND EFFECTIVENESS

EFFICACY

Critical (worm count) studies in dogs demonstrated that pyrantel pamoate at the recommended dosage is highly efficacious against T. leonina (99%), T. canis (85%), A. caninum (97%), and U. stenocephala (94%).

SAFETY

One of the most outstanding and significant features of pyrantel pamoate is its wide margin of therapeutic safety in dogs. The acute oral LD50 of pyrantel pamoate administered in gelatin capsules to female and male dogs is greater than 314 mg base per pound of body weight, which indicates a therapeutic index in excess of 138 X the recommended dosage. In subacute and chronic studies, no significant morphological abnormalities could be attributed to pyrantel pamoate when administered to dogs at daily dose rates up to 94 mg base per pound of body weight (40 x) for periods of 19, 30, and 90 days. Clinical studies conducted in a wide variety of geographic locations using more than 40 different breeds of dogs showed no drug-induced toxic effects. Included in these studies were nursing pups, weaned pups, adults, pregnant bitches and males at stud. Additional data have demonstrated the safe use of pyrantel pamoate in (1) dogs having heartworm infections and/or receiving medication for heartworms, (2) dogs exposed to organophosphate flea collars or flea/tick dip treatments, and (3) dogs undergoing concurrent treatment or medication at the time of worming such as immunization and antibacterial treatment.

If you have any questions or comments about this product, please write: SENTRY Consumer Response, PO Box 540399, Omaha, NE 68154-0399.

Distributed by:

Sergeant's Pet Care Products, Inc., Omaha, NE 68138